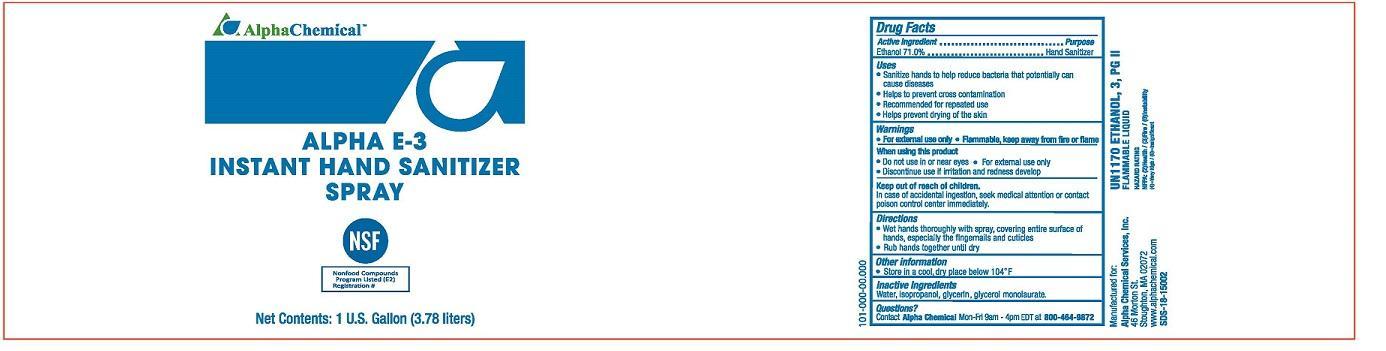 DRUG LABEL: Alpha E-3 Instant Hand Sanitizer
NDC: 69335-002 | Form: SPRAY
Manufacturer: Alpha Chemical Services, Inc.
Category: otc | Type: HUMAN OTC DRUG LABEL
Date: 20241216

ACTIVE INGREDIENTS: ALCOHOL 710 g/1000 mL
INACTIVE INGREDIENTS: WATER; GLYCERYL LAURATE; GLYCERIN

Alpha E-3 Instant Hand Sanitizer Spray 69335-002

Active Ingredient

Ethanol 71.0%

Purpose

Hand Sanitizer

Uses

- Sanitize hands to help reduce bacteria that potentially can cause disease
- Helps to prevent cross contamination
- Recommended for repeated use
- Helps to prevent drying of the skin

Warnings

- For external use only
- Flammable, keep away from fire or flame

When using this product

- Do not use in or near eyes
- For external use only
- Discontinue use if irritation and redness develop

Keep out of reach of children

In case of accidental ingestion, seek medical attention or contact a poison control center immediately.

Directons

- Wet hands thoroughly with spray, covering entire surface of hands, especially the fingernails and cuticles
- Rub hands together until dry

Other information

- Store in a cool, dry place below 104° F

Inactive ingredients

water, isopropanol, glycerin, glycerol monolaurate

Questions?

Contact Alpha Chemical Mon-Fri 9am - 4p PST at 800-464-9872

Manufactured for:

Alpha Chemical Services, Inc.

46 Morton St.

Stoughton, MA 02072

www.alphachemical.com

SDS-18-15002

Principal Display Panel

NDC: 69335-002-01

Alpha E-3 Instant Hand Sanitizer Spray

NSF

Nonfood Compounds Program Listed (E2) Registration #